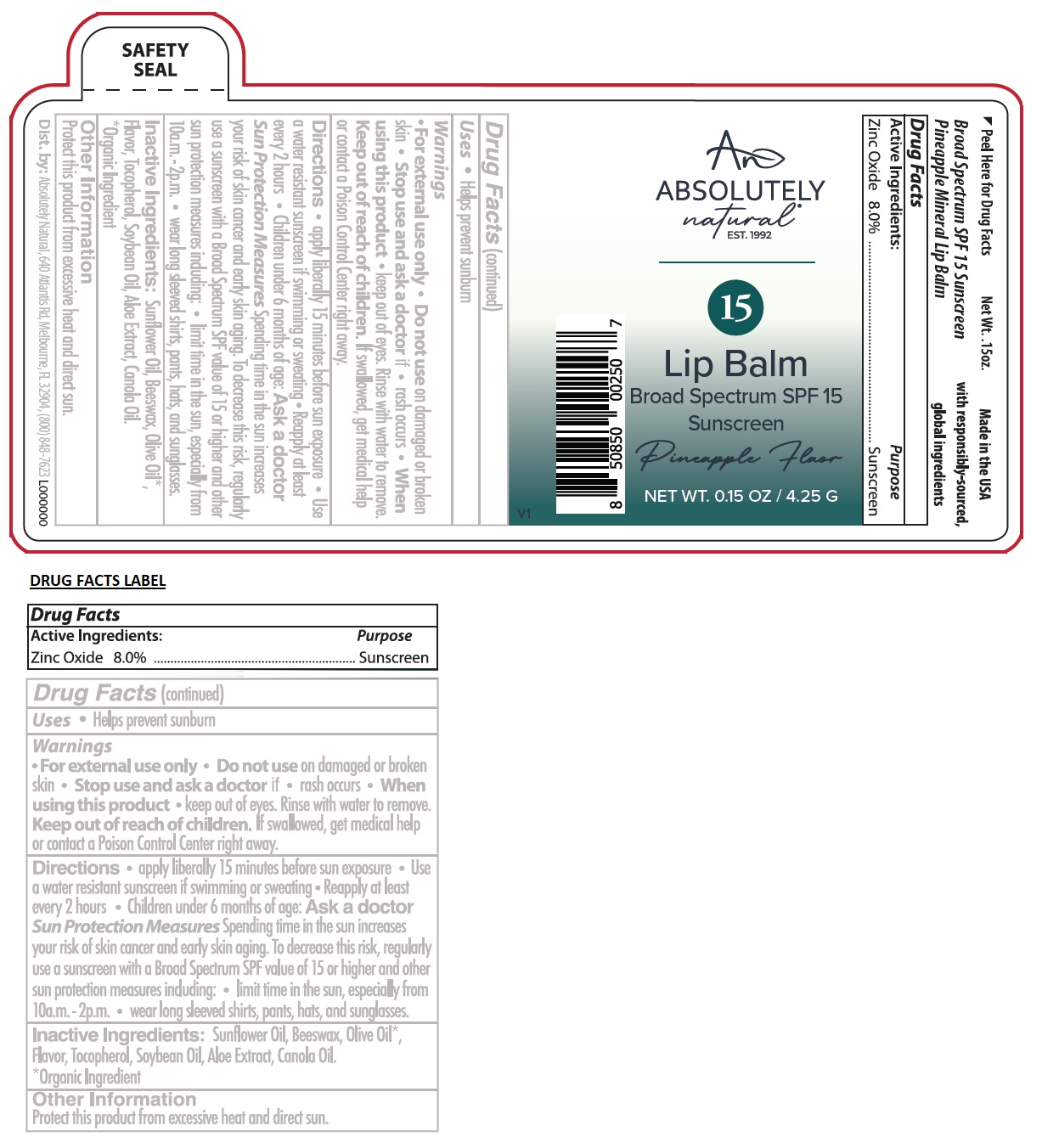 DRUG LABEL: ABSOLUTELY natural Lip Balm Broad Spectrum SPF 15 Sunscreen
NDC: 70793-043 | Form: STICK
Manufacturer: Absolutely Natural
Category: otc | Type: HUMAN OTC DRUG LABEL
Date: 20240923

ACTIVE INGREDIENTS: ZINC OXIDE 8 g/100 g
INACTIVE INGREDIENTS: SUNFLOWER OIL; WHITE WAX; OLIVE OIL; TOCOPHEROL; SOYBEAN OIL; ALOE VERA LEAF; CANOLA OIL

ABSOLUTELY natural Lip Balm Broad Spectrum SPF 15 Sunscreen

Active Ingredients:

Zinc Oxide 8.0%

Purpose

Sunscreen

Uses

• Helps prevent sunburn

Warnings

• For external use only • Do not use on damaged or broken skin • Stop use and ask a doctor if • rash occurs • When using this product • keep out of eyes. Rinse with water to remove.

Keep out of reach of children. If swallowed, get medical help or contact a Poison Control Center right away.

Directions

• apply liberally 15 minutes before sun exposure • Use a water resistant sunscreen if swimming or sweating • Reapply at least every 2 hours • Children under 6 months of age: Ask a doctor Sun Protection Measures Spending time in the sun increases your risk of skin cancer and early skin aging. To decrease this risk, regularly use a sunscreen with a Broad Spectrum SPF value of 15 or higher and other sun protection measures including: • limit time in the sun, especially from 10a.m - 2p.m • wear long sleeved shirts, pants, hats, and sunglasses.

Inactive Ingredients:

Sunflower Oil, Beeswax, Olive Oil*, Flavor, Tocopherol, Soybean Oil, Aloe Extract, Canola Oil.

*Organic Ingredient

Other Information

Protect this product from excessive heat and direct sun.

Pineapple Flavor

Pineapple Mineral Lip Balm

Made in the USA with responsibly-sourced global ingredients

Dist. by: Absolutely Natural, 640 Atlantis Rd, Melbourne, FL 32904, (800) 848-7623